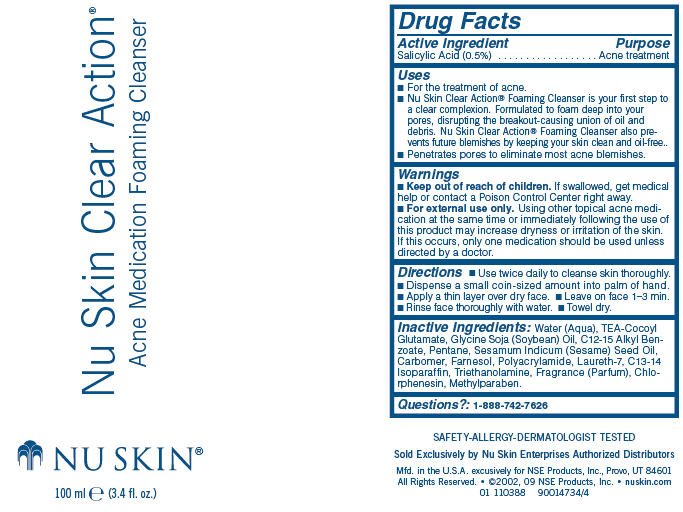 DRUG LABEL: Nu Skin Clear Action
NDC: 62839-0388 | Form: LOTION
Manufacturer: NSE Products, Inc.
Category: otc | Type: HUMAN OTC DRUG LABEL
Date: 20181221

ACTIVE INGREDIENTS: Salicylic Acid 5 g/1000 mL
INACTIVE INGREDIENTS: Water; Soybean Oil; Alkyl (C12-15) Benzoate; Pentane; Sesame Oil; FARNESOL, (2E,6E)-; Laureth-7; C13-14 Isoparaffin; Trolamine; Chlorphenesin; Methylparaben

Nu Skin Clear Action®
Acne Medication Foaming Cleanser

Drug Facts

Active Ingredient

Salicylic Acid (0.5%)

Purpose

Acne treatment

Uses

- For the treatment of acne.
- Nu Skin Clear Action® Foaming Cleanser is your first step to a clear complexion. Formulated to foam deep into your pores, disrupting the breakout-causing union of oil and debris. Nu Skin Clear Action® Foaming Cleanser also prevents future blemishes by keeping your skin clean and oil-free..
- Penetrates pores to eliminate most acne blemishes.

Warnings

- Keep out of reach of children. If swallowed, get medical help or contact a Poison Control Center right away.

WHEN USING

- For external use only. Using other topical acne medication at the same time or immediately following the use of this product may increase dryness or irritation of the skin. If this occurs, only one medication should be used unless directed by a doctor.

Directions

- Use twice daily to cleanse skin thoroughly.
- Dispense a small coin-sized amount into palm of hand.
- Apply a thin layer over dry face.
- Leave on face 1–3 min.
- Rinse face thoroughly with water.
- Towel dry.

Inactive Ingredients

Water (Aqua), TEA-Cocoyl Glutamate, Glycine Soja (Soybean) Oil, C12-15 Alkyl Benzoate, Pentane, Sesamum Indicum (Sesame) Seed Oil, Carbomer, Farnesol, Polyacrylamide, Laureth-7, C13-14 Isoparaffin, Triethanolamine, Fragrance (Parfum), Chlorphenesin, Methylparaben.

Questions?

1-888-742-7626

PRINCIPAL DISPLAY PANEL - 100 ml Bottle Label

Nu Skin Clear Action®

Acne Medication Foaming Cleanser

NU SKIN®

100 ml e (3.4 fl. oz.)